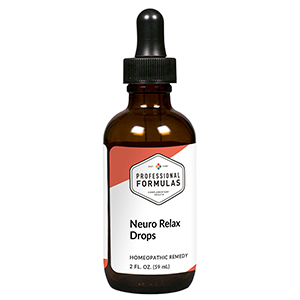 DRUG LABEL: Neuro Relax Drops
NDC: 63083-2055 | Form: LIQUID
Manufacturer: Professional Complementary Health Formulas
Category: homeopathic | Type: HUMAN OTC DRUG LABEL
Date: 20190815

ACTIVE INGREDIENTS: AVENA SATIVA FLOWERING TOP 1 [hp_X]/59 mL; ARTEMISIA ANNUA FLOWERING TOP 1 [hp_X]/59 mL; HOPS 1 [hp_X]/59 mL; VALERIAN 1 [hp_X]/59 mL; PASSIFLORA INCARNATA FLOWERING TOP 2 [hp_X]/59 mL; SCUTELLARIA LATERIFLORA WHOLE 2 [hp_X]/59 mL; GELSEMIUM SEMPERVIRENS ROOT 6 [hp_X]/59 mL; STRYCHNOS IGNATII SEED 6 [hp_X]/59 mL; PULSATILLA MONTANA WHOLE 6 [hp_X]/59 mL; ZINC 12 [hp_X]/59 mL
INACTIVE INGREDIENTS: ALCOHOL; WATER

C55

ACTIVE INGREDIENTS

Avena sativa 1X
Chamomilla 1X
Humulus lupulus 1X
Valeriana officinalis 1X
Passiflora incarnata 2X
Scutellaria lateriflora 2X
Gelsemium sempervirens 6X
Ignatia amara 6X
Pulsatilla 6X
Zincum metallicum 12X

QUESTIONS

Professional Formulas

PO Box 2034 Lake Oswego, OR 97035

INDICATIONS

For the temporary relief of anxiousness, restlessness, racing thoughts, excessive worry, poor concentration, or stress.*

PURPOSE

*Claims based on traditional homeopathic practice, not accepted medical evidence. Not FDA evaluated.

WARNINGS

In case of overdose, get medical help or contact a poison control center right away.

Keep out of the reach of children.

PREGNANCY OR BREAST FEEDING

If pregnant or breastfeeding, ask a healthcare professional before use.

DIRECTIONS

Place drops under tongue 30 minutes before/after meals. Adults and children 12 years and over: Take 10 drops up to 3 times per day for up to 6 weeks. For immediate onset of symptoms, take 10 to 15 drops every 15 minutes up to 3 hours. For less severe symptoms, take 10-15 drops hourly up to 8 hours. Consult a physician for use in children under 12 years of age.

OTHER INFORMATION

Tamper resistant. If seal is broken, do not use. After opening, close container tightly and store at room temperature away from heat.

INACTIVE INGREDIENTS

20% ethanol, purified water.

LABEL

Est 1985

Professional Formulas

Complementary Health

Neuro Relax Drops

Homeopathic Remedy

2 FL. OZ. (59 mL)